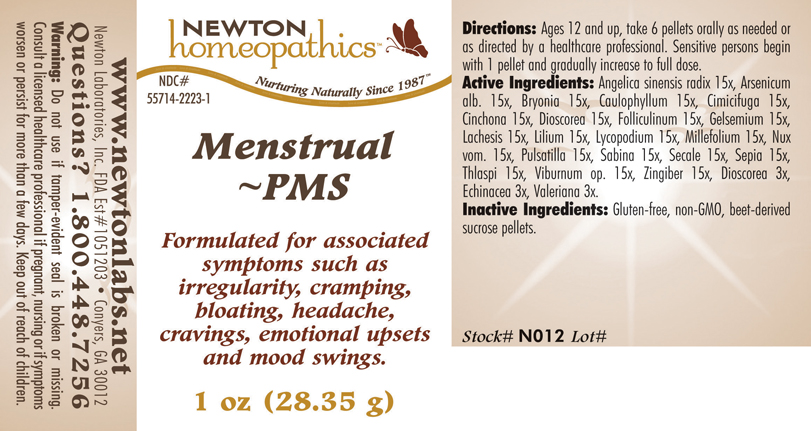 DRUG LABEL: Menstrual - PMS 
NDC: 55714-2223 | Form: PELLET
Manufacturer: Newton Laboratories, Inc.
Category: homeopathic | Type: HUMAN OTC DRUG LABEL
Date: 20110301

ACTIVE INGREDIENTS: Angelica Sinensis Root 15 [hp_X]/1 g; Arsenic Trioxide 15 [hp_X]/1 g; Bryonia Alba Root 15 [hp_X]/1 g; Caulophyllum Thalictroides Root 15 [hp_X]/1 g; Black Cohosh 15 [hp_X]/1 g; Cinchona Officinalis Bark 15 [hp_X]/1 g; Dioscorea Villosa Tuber 15 [hp_X]/1 g; Estrone 15 [hp_X]/1 g; Gelsemium Sempervirens Root 15 [hp_X]/1 g; Lachesis Muta Venom 15 [hp_X]/1 g; Lilium Lancifolium Whole Flowering 15 [hp_X]/1 g; Lycopodium Clavatum Spore 15 [hp_X]/1 g; Achillea Millefolium 15 [hp_X]/1 g; Strychnos Nux-vomica Seed 15 [hp_X]/1 g; Pulsatilla Vulgaris 15 [hp_X]/1 g; Juniperus Sabina Leafy Twig 15 [hp_X]/1 g; Claviceps Purpurea Sclerotium 15 [hp_X]/1 g; Sepia Officinalis Juice 15 [hp_X]/1 g; Capsella Bursa-pastoris 15 [hp_X]/1 g; Viburnum Opulus Bark 15 [hp_X]/1 g; Ginger 15 [hp_X]/1 g; Echinacea, Unspecified 3 [hp_X]/1 g; Valerian 3 [hp_X]/1 g
INACTIVE INGREDIENTS: Sucrose

Menstrual - PMS

INDICATIONS & USAGE SECTION

Menstrual - PMS Formulated for associated symptoms such as irregularity, cramping, bloating, headache, cravings, emotional upsets and mood swings.

DOSAGE & ADMINISTRATION SECTION

Directions: Ages 12 and up, take 6 pellets orally as needed or as directed by a healthcare professional. Sensitive persons begin with 1 pellet and gradually increase to full dose.

OTC - ACTIVE INGREDIENT SECTION

Angelica sinensis radix 15x, Arsenicum alb. 15x, Bryonia 15x, Caulophyllum 15x, Cimicifuga 15x, Cinchona 15x, Dioscorea 15x, Folliculinum 15x, Gelsemium 15x, Lachesis 15x, Lilium 15x, Lycopodium 15x, Millefolium 15x, Nux vom. 15x, Pulsatilla 15x, Sabina 15x, Secale 15x, Sepia 15x, Thlaspi 15x, Viburnum op. 15x, Zingiber 15x, Dioscorea 3x, Echinacea 3x, Valeriana 3x.

OTC - PURPOSE SECTION

Formulated for associated symptoms such as irregularity, cramping, bloating, headache, cravings, emotional upsets and mood swings.

INACTIVE INGREDIENT SECTION

Inactive Ingredients: Gluten-free, non-GMO, beet-derived sucrose pellets.

QUESTIONS SECTION

www.newtonlabs.net Newton Laboratories, Inc. FDA Est # 1051203 - Conyers, GA 30012
Questions? 1.800.448.7256

WARNINGS SECTION

Warning: Do not use if tamper - evident seal is broken or missing. Consult a licensed healthcare professional if pregnant, nursing or if symptoms worsen or persist for more than a few days. Keep out of reach of children.

OTC - PREGNANCY OR BREAST FEEDING SECTION

Consult a licensed healthcare professional if pregnant, nursing or if symptoms worsen or persist for more than a few days.

OTC - KEEP OUT OF REACH OF CHILDREN SECTION

Keep out of reach of children.